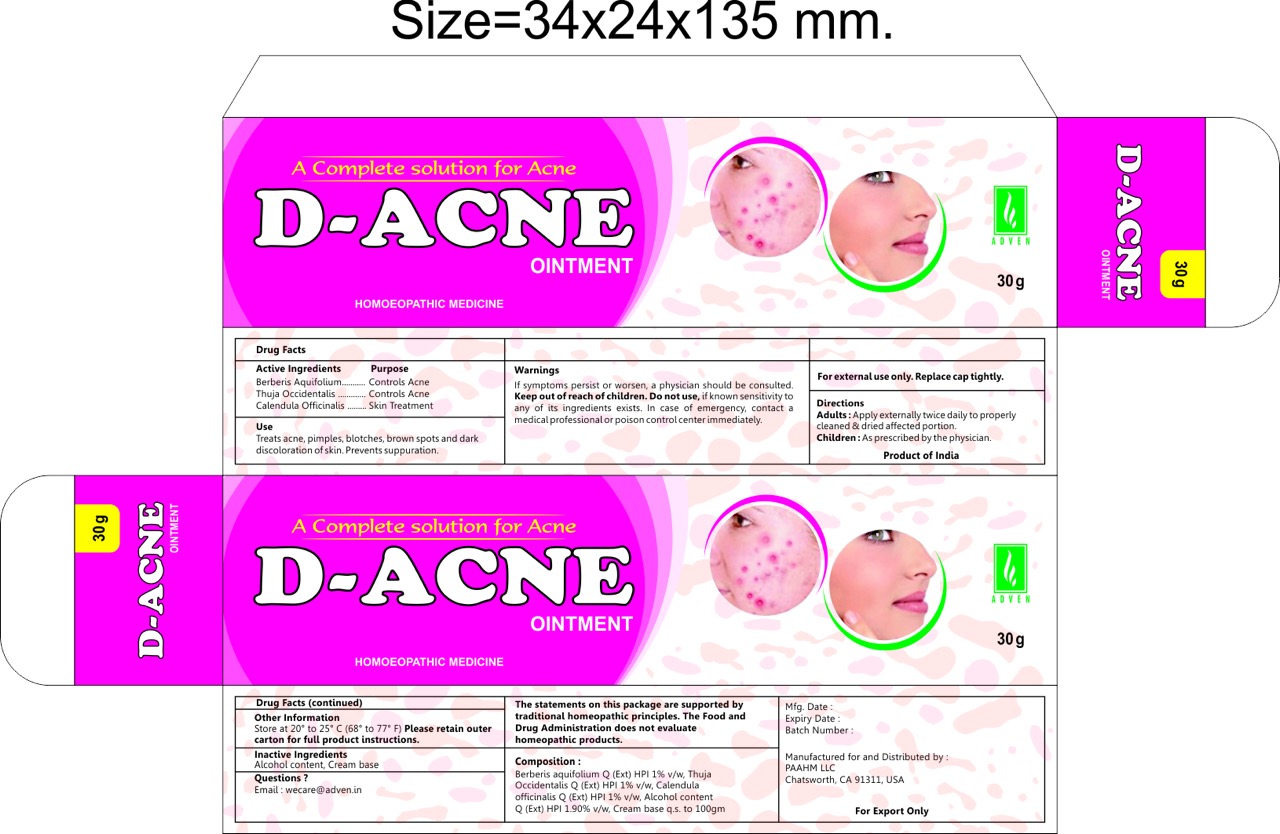 DRUG LABEL: d-acne
NDC: 69825-005 | Form: OINTMENT
Manufacturer: Adven Biotech Private Limited
Category: homeopathic | Type: HUMAN OTC DRUG LABEL
Date: 20160328

ACTIVE INGREDIENTS: THUJA OCCIDENTALIS ROOT 1 [hp_X]/100 g; MAHONIA AQUIFOLIUM ROOT 1 [hp_X]/100 g; CALENDULA OFFICINALIS FLOWER 1 [hp_X]/100 g
INACTIVE INGREDIENTS: ALCOHOL

D Acne Cream

DOSAGE AND ADMINISTRATION

Adults: Apply externally twice daily to properly cleaned & dried affected portion.

Children under 18 years: As prescribed by the physician.

WARNINGS

If symptons persist or worsen, a physician should be consulted. Keep out of reach of children. Do not use, if known sentivity to any of its ingredients exists. In case of emergency, contact a medical professional or posion control center immediately. For external use only. Replace cap tightly.

PURPOSE

Controls Acne

Skin Treatment

INACTIVE INGREDIENT

Alcohol content, Cream base

ACTIVE INGREDIENT

Berberis Aquifolium, Thuja Occidentalis, Calendula Officinalis

INDICATIONS AND USAGE

Treats acne, pimples, blotches, brown spots and dark discoloration of skin. Prevents suppuration.